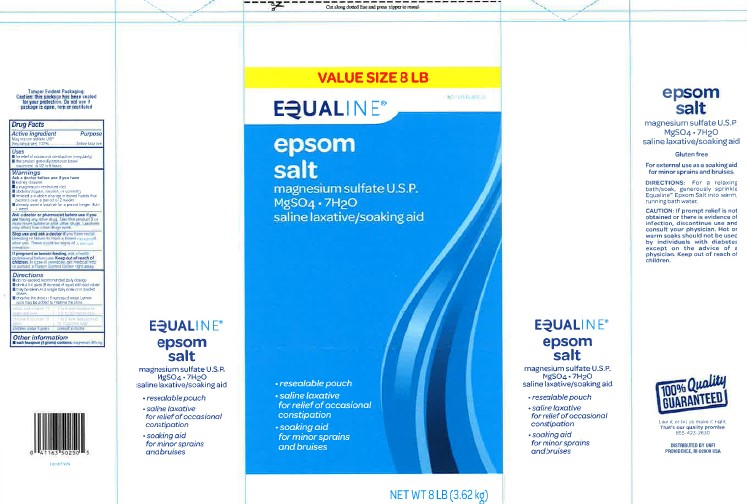 DRUG LABEL: Epsom Salt
NDC: 41163-602 | Form: GRANULE, FOR SOLUTION
Manufacturer: United Natural Foods, Inc. dba UNFI
Category: otc | Type: HUMAN OTC DRUG LABEL
Date: 20260217

ACTIVE INGREDIENTS: MAGNESIUM SULFATE HEPTAHYDRATE 1 g/1 g

Equaline 602.002/602AA
Epsom Salt

Tamper Evident Statement

Tamper Evident Packaging

Caution: this package has been sealed for your protection. Do not use if package is open, torn or mulitated.

Active ingredient

Magnesium sulfate USP (heptahydrate) 100%

Purpose

Saline Laxative

Uses

- for relief of occasional constipation (irregularity)
- for this product generally produces bowel movement in 1/2 to 6 hours

Warning

for this product

Ask a doctor before use if you have

- kidney disease
- a magnesium-restricted diet
- abdominal pain, nausea, or vomiting
- noticed a sudden change in bowel habits that persists over a period of 2 weeks
- already used a laxative for a period longer than 1 week

Ask a doctor or pharmacist before use if you are

taking any other drug. Take this product 2 or more hours before or after other drugs. Laxatives may affect how other drugs work.

Stop use and ask a doctor if

you have rectal bleeding or failure to have a bowel movement after use. These could be signs of a serious condition.

If pregnant or breast-feeding,

ask a health professional before use.

Keep out of reach of children.

In case of overdose, get medical help or contact a Poison Control Center right away.

Directions

- do not exceed recommended daily dosage
- drink a full glass (8 ounces) of liquid with each dose
- may be taken as a single daily dose or in divided doses
- dissolve the dose in 8 ounces of water. Lemon juice may be added to improve the taste.

adults and children 12 years and over - 2 to 6 level teaspoons (10 to 30 grams) daily

children 6 to under 12 years - 1 to 2 level teaspoons (5 to 10 grams) daily

children under 6 years - consult a doctor

Other information

- each teaspoon (5 grams) contains: magnesium 495 mg

Inactive Ingredient

None

Side Panel

EQUALINE

epsom salt

magnesium sulfate U.S.P.

MgSO4 • 7H20

saline laxative/soaking aid

- resealable pouch
- saline laxative for relief of occasional constipation
- soaking aid for minor sprains and bruises

Gluten free

For external use as a soaking aid for minor sprains and bruises

DIRECTIONS: For a relaxing bath/soak, generously sprinkle Equaline®Epsom Salt into warm, running bath water.

Caution: If prompt relief is not obtained or there is evidence of infection, discontinue use and consult your physician. Hot or warm soaks should not be used by individuals with diabetes except on the advice of a physician. Keep out of reach of children.

ADVERSE REACTION

100% Quality Guaranteed

Like it or let us make it right.

That's our quality promise.

855-423-2630

Please have package available.

DISTRIBUTED BY UNFI

PROVIDENCE, RI 02908 USA

Principal display panel

Cut along dotted line and press zipper to reseal.

VALUE SIZE 8 LB

NDC 41163-602-80

EQUALINE®

epsom salt

magnesium sulfate U.S.P.

MgSO4• 7H20

saline laxative/soaking aid

- resealable pouch
- saline laxative for relief of occasional constipation
- soaking aid for minor sprains and bruises

NET WT 8 LB (3.62 kg)